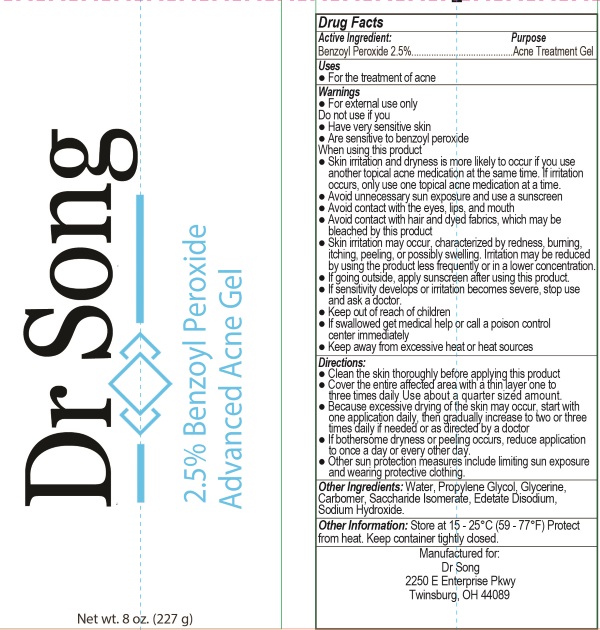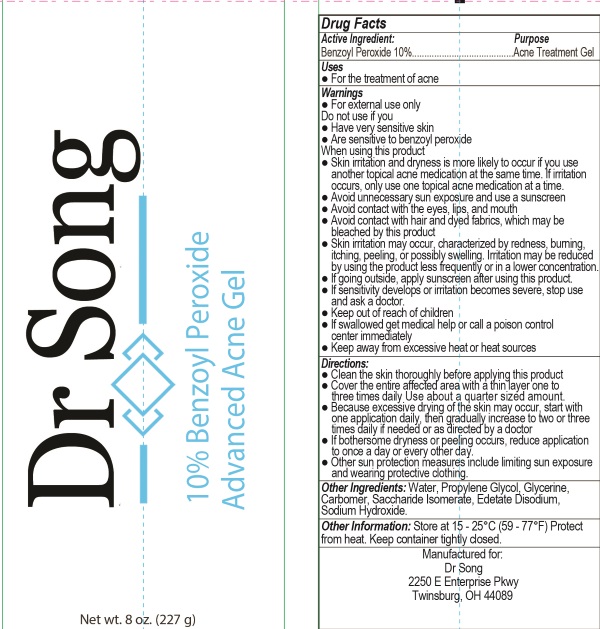 DRUG LABEL: Dr Song Acne
NDC: 71174-100 | Form: GEL
Manufacturer: Secret By Nature LLC
Category: otc | Type: HUMAN OTC DRUG LABEL
Date: 20170112

ACTIVE INGREDIENTS: BENZOYL PEROXIDE 25 mg/1 g
INACTIVE INGREDIENTS: CARBOMER INTERPOLYMER TYPE A (55000 CPS); EDETATE DISODIUM; GLYCERIN; PROPYLENE GLYCOL; SACCHARIDE ISOMERATE; SODIUM HYDROXIDE; WATER

Dr Song Acne

ACTIVE INGREDIENT

Active | Purpose
BENZOYL PEROXIDE | Acne Treatment

INACTIVE INGREDIENT

CARBOMER,EDETATE DISODIUM, GLYCERINE, PROPYLENE GLYCOL, SACCHARIDE ISOMERATE, SODIUM HYDROXIDE, WATER

KEEP OUT OF REACH OF CHILDREN

If swallowed, get medical help or contact a Poison Control Center right away.

INDICATIONS & USAGE

For the treatment of acne

WARNINGS

For external use only.

- Avoid unnecessary sun exposure and use a sunscreen
- Avoid contact with the eyes, lips, and mouth
- Avoid contact with hair and dyed fabrics, which may be bleached by this product
- Skin irritation may occur, characterized by redness, burning, itching, peeling, or possibly swelling. Irritation may be reduced by using the product less frequently or in a lower concentration.
- If going outside, apply sunscreen after using this product.
- Keep away from excessive heat or heat sources

Do to use if you:

- Have very sensitive skin
- Are sensitive to benzoyl peroxide.

When using this product

- Skin irritation and dryness is more likely to occur if you use another topical acne medication at the same time. If irritation occurs, only use one topical acne medication at a time.

DIRECTIONS

- Clean the skin thoroughly before applying this product
- Cover the entire affected area with a thin layer one to three times daily Use about a quarter sized amount.
- Because excessive drying of the skin may occur, start with one application daily, then gradually increase to two or three times daily if needed or as directed by a doctor
- If bothersome dryness or peeling occurs, reduce application to once a day or every other day.
- Other sun protection measures include limiting sun exposure and wearing protective clothing.

PURPOSE

For the treatment of acne.

Stop use and ask a doctor if:

Sensitivity develops or irritation becomes severe, stop us and ask a doctor.

Distributed By:

Dr Song,

2250 E Enterprise Pkwy

TWINSBURG, OH, 44089

Other Information:

Store: At Room Temperature 15° - 25°C (59°- 77°F). Protect from heat. Keep container tightly closed.